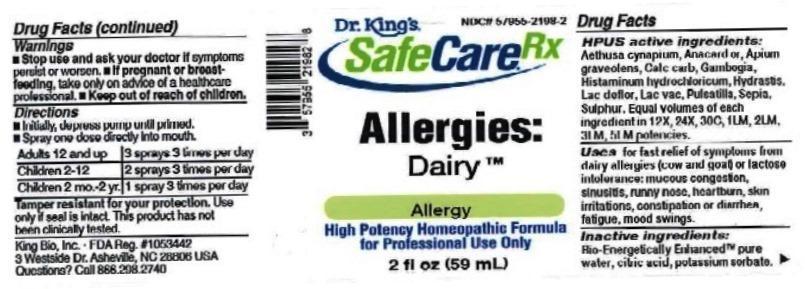 DRUG LABEL: Allergies Dairy
NDC: 57955-2198 | Form: LIQUID
Manufacturer: King Bio Inc.
Category: homeopathic | Type: HUMAN OTC DRUG LABEL
Date: 20161219

ACTIVE INGREDIENTS: SEMECARPUS ANACARDIUM JUICE 12 [hp_X]/59 mL; AETHUSA CYNAPIUM 12 [hp_X]/59 mL; CELERY SEED 12 [hp_X]/59 mL; OYSTER SHELL CALCIUM CARBONATE, CRUDE 12 [hp_X]/59 mL; GAMBOGE 12 [hp_X]/59 mL; HISTAMINE DIHYDROCHLORIDE 12 [hp_X]/59 mL; GOLDENSEAL 12 [hp_X]/59 mL; SKIM MILK 12 [hp_X]/59 mL; COW MILK 12 [hp_X]/59 mL; PULSATILLA VULGARIS 12 [hp_X]/59 mL; SEPIA OFFICINALIS JUICE 12 [hp_X]/59 mL; SULFUR 12 [hp_X]/59 mL
INACTIVE INGREDIENTS: WATER; ANHYDROUS CITRIC ACID; POTASSIUM SORBATE

Allergies: Dairy

ACTIVE INGREDIENT

Drug Facts__________________________________________________________________________________________________________

HPUS active ingredients: Aethusa cynapium, Anacardium orientale, Apium graveolens, Calcarea carbonica, Gambogia, Histaminum hydrochloricum, Hydrastis canadensis, Lac defloratum, Lac vaccinum, Pulsatilla, Sepia, Sulphur. Equal volumes of each ingredient in 12X, 24X, 30C, 1LM, 2LM, 3LM, 5LM potencies.

INDICATIONS AND USAGE

Uses for fast relief of symptoms from dairy allergies (cow & goat) or lactose intolerance: mucous congestion, sinusitis, runny nose, heartburn, skin irritations, earaches, constipation or diarrhea, fatigue, mood swings.

Inactive Ingredients:

Bio-Energetically Enhanced™ pure water, citric acid and potassium sorbate.

Warnings

- Stop use and ask your doctor if symptoms persist or worsen.
- If pregnant or breast-feeding, take only on advice of a healthcare professional.

- Keep out of reach of children.

Directions

- Initially, depress pump until primed.
- Spray one dose directly into mouth.
- Adults 12 and up: 3 sprays 3 times per day.
- Children 2-12: 2 sprays 3 times per day.
- Children 2 mo-2yr: 1 spray 3 times per day.

OTHER SAFETY INFORMATION

Tamper resistant for your protection. Use only if seal is intact. This product has not been clinically tested.

PURPOSE

Uses for fast relief of symptoms from dairy allergies (cow & goat) or lactose intolerance:

- mucous congestion
- sinusitis
- runny nose
- heartburn
- skin irritations
- earaches
- constipation or diarrhea
- fatigue
- mood swings